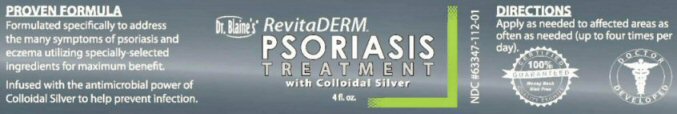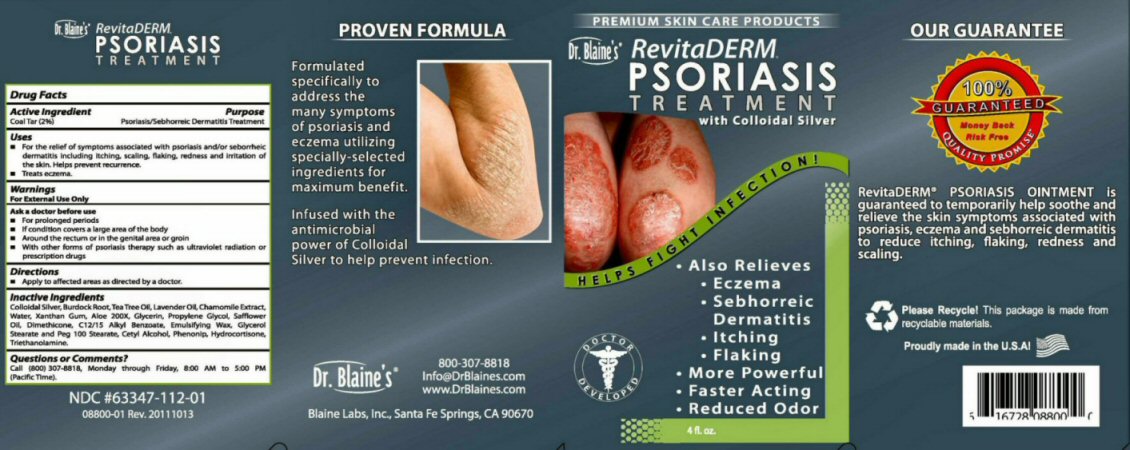 DRUG LABEL: RevitaDERM PSORIASIS
NDC: 63347-112 | Form: OINTMENT
Manufacturer: Blaine Labs Inc.
Category: otc | Type: HUMAN OTC DRUG LABEL
Date: 20231221

ACTIVE INGREDIENTS: COAL TAR 2 mg/100 mL
INACTIVE INGREDIENTS: SILVER; ARCTIUM LAPPA ROOT; TEA TREE OIL; LAVENDER OIL; CHAMAEMELUM NOBILE FLOWER; WATER; XANTHAN GUM; ALOE; GLYCERIN; PROPYLENE GLYCOL; SAFFLOWER OIL; DIMETHICONE; ALKYL (C12-15) BENZOATE; CETOSTEARYL ALCOHOL; GLYCERYL MONOSTEARATE; PEG-100 STEARATE; CETYL ALCOHOL; HYDROCORTISONE; TROLAMINE; PHENOXYETHANOL; METHYLPARABEN; BUTYLPARABEN; ETHYLPARABEN; PROPYLPARABEN

Active Ingredients Section

Drug Facts Active Ingredient Coal Tar (2%)

Purpose Section

Purpose Psoriasis/Sebhorreic Dermatitis Treatment

Keep Out of Reach Of Children Section

Enter section text here

Uses Section

Uses For the relief of symptoms associated with psoriasis and or seborrheic dermatitis including itching, scaling, flaking, redness and irritation of the skin. Helps prevent recurrences.

Treats eczema.

Warnings Section

Warnings For external use only.

Ask a doctor before use For prolonged periods If condition covers a large area of the body Around the rectum or in the genital area or groin With other forms of psoriasis therapy such as ultraviolet radiation or prescription drugs.

Directions Section

Directions Apply to affected areas as directed by a doctor.

Apply as needed to affected areas as often as needed (up to four times per day)

Inactive Ingredient Section

Inactive Ingredients Colloidal Silver, Burdock Root, Tea Tree Oil, Lavender Oil, Chamomile Extract, Water, Xanthan Gum, Aloe 200X, Glycerin, Propylene Glycol, Safflower Oil, Dimethicone, C12/15 Alky Benzoate, Emulsifying Wax, Glycerol Stearate and PEG 100 Stearate, Cetyl Alcohol, Phenonip (phenoxyethanol, methylparaben, butylparaben, ethylparaben, propylparaben), Hydrocortisone, Triethanolamine.

Questions or Comments? Section

Questions or Comments? Call (800) 307-8818, Monday through Friday, 8:00 AM to 5:00 PM (Pacific Time)

Package Label Section

Dr. Blaine's RevitaDERM PSORIASIS TREATMENT

NDC #63347-112-01 08800-01 Rev 20111013

PROVEN FORMULA

Formulated specifically to address the many symptoms of psoriasis and eczema utilizing specially selected ingredients for maximum benefit.

Infused with the antimicrobial power of Colloidal Silver to help prevent infection.

Dr. Blaine's 800 307-8818 info@DrBlaines.com www.DrBlaines.com Blaine Labs, Inc. Santa Fe Springs, CA 90670

PREMIUM SKIN CARE PRODUCTS HELPS FIGHT INFECTION

Also Relieves Eczema Sebhorreic Dermatitis Itching Flaking More Powerful Faster Acting Reduce Odor DOCTOR DEVELOPED

4 fl. oz

OUR GUARANTEE 100% GUARANTEED Money Back Rick Free QUALITY PROMISE

RevitaDerm PSORIIASIS OINTMENT is guaranteed to temporarily help soothe and relieve the kin symptoms associated with psoriasis, eczema, and sebhorreic dermatitis to reduce itching, flaking, redness, and scaling.

Please Recycle! This package is made from recyclable materails. Proudly made in the U.S.A.

res